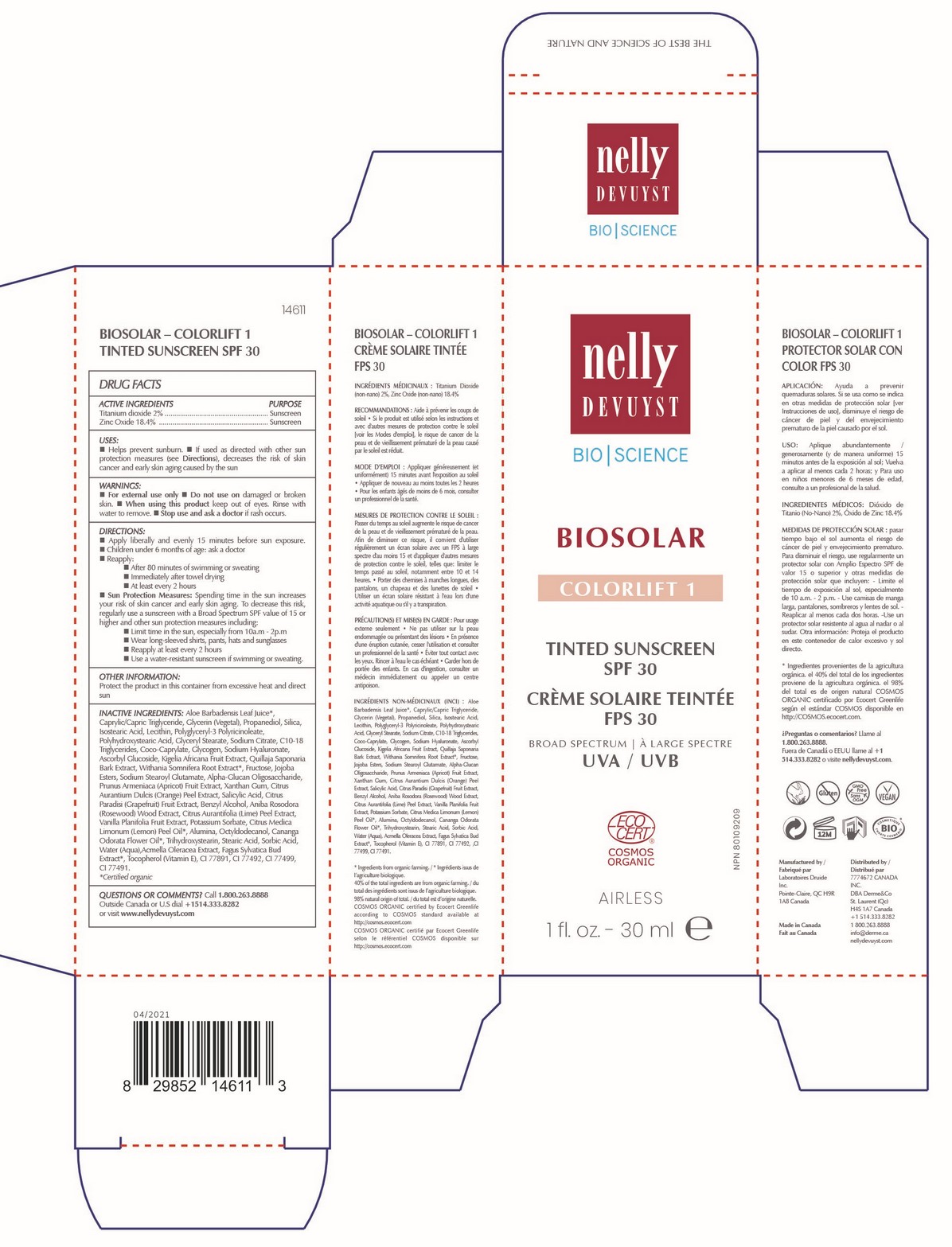 DRUG LABEL: NELLY DEVUYST BIOSOLAR COLORLIFT 1 TINTED SUNSCREEN 30 mL
NDC: 71447-032 | Form: CREAM
Manufacturer: LABORATOIRES DRUIDE INC
Category: otc | Type: HUMAN OTC DRUG LABEL
Date: 20210426

ACTIVE INGREDIENTS: TITANIUM DIOXIDE 2 g/100 g; ZINC OXIDE 18.4 g/100 g
INACTIVE INGREDIENTS: PROPANEDIOL; FAGUS SYLVATICA FLOWER BUD; SILICON DIOXIDE; CANANGA OIL; LIME PEEL; FRUCTOSE; TRIHYDROXYSTEARIN; ANIBA ROSAEODORA WOOD; CAPRYLIC/CAPRIC/LINOLEIC TRIGLYCERIDE; GLYCERYL MONOSTEARATE; FERRIC OXIDE YELLOW; ACMELLA OLERACEA FLOWERING TOP; C10-18 TRIGLYCERIDES; SODIUM CITRATE; FERRIC OXIDE RED; TOCOPHEROL; POTASSIUM SORBATE; ALOE VERA LEAF; COCO-CAPRYLATE; ALUMINUM OXIDE; GLYCERIN; STEARIC ACID; XANTHAN GUM; LECITHIN, SUNFLOWER; POLYHYDROXYSTEARIC ACID (2300 MW); POLYGLYCERYL-3 PENTARICINOLEATE; SALICYLIC ACID; BENZYL ALCOHOL; ISOSTEARIC ACID; FERROSOFERRIC OXIDE; APRICOT; .ALPHA.-GLUCAN OLIGOSACCHARIDE; SODIUM STEAROYL GLUTAMATE; QUILLAJA SAPONARIA BARK; GLYCOGEN; SORBIC ACID; OCTYLDODECANOL; VANILLA PLANIFOLIA OIL; JOJOBA OIL, RANDOMIZED; KIGELIA AFRICANA FRUIT; HYALURONATE SODIUM; LEMON OIL, COLD PRESSED; GRAPEFRUIT PEEL; ORANGE PEEL; WITHANIA SOMNIFERA ROOT; ASCORBYL GLUCOSIDE

NELLY DEVUYST BIOSOLAR COLORLIFT 1 TINTED SPF 30 SUNSCREEN 30 mL

Active Ingredients

Titanium Dioxide 2.0%

Zinc Oxide 18.4%

Purpose

Sunscreen

Uses

▪ Helps prevent sunburn. ▪ If used as directed with other sun protection measures (see Directions), decreases the risk of skin cancer and early skin aging caused by the sun.

Warnings

For external use only

When using this product

keep out of eyes. Rinse with water to remove.

Stop use and ask a doctor if

rash occurs.

Keep out of reach of children

If swallowed, get medical help or contact Poison Control Center right away.

Directions

▪ Apply liberally and evenly 15 minutes before sun exposure ▪ Reapply ▪ After 80 minutes of swimming or sweating ▪ Immediately after towel drying ▪ At least every 2 hours ▪ Sun Protection Measures ▪ Spending time in the sun increases your risk of skin cancer and early skin aging. To decrease this risk, regularly use a sunscreen with a Broad Spectrum SPF value of 15 or higher and other sun protection measures including: ▪ Limit time in the sun, especially from 10 a.m. - 2 p.m. ▪ Wear long-sleeved shirts, pants, hats, and sunglasses ▪ Use a water-resistant sunscreen if swimming or sweating.

Other Information

Protect the product in this container from excessive heat and direct sun.

Inactive Ingredients

Aloe Barbadensis Leaf Juice*, Caprylic/Capric Triglyceride, Glycerin (Vegetal), Propanediol, Silica, Isostearic Acid, Lecithin, Polyglyceryl-3 Polyricinoleate, Polyhydroxystearic Acid, Glyceryl Stearate, Sodium Citrate, C10-18 Tryglycerides, Coco-Caprylate, Glycogen, Sodium Hyaluronate, Ascorbyl Glucoside, Kigelia Africana Fruit Extract, Quillaja Saponaria Bark Extract, Withania Somnifera Root Extract*, Fructose, Jojoba Esters, Sodium Stearoyl Glutamate, Alpha-Glucan Oligosaccharide, Prunus Armeniaca (Apricot) Fruit Extract, Xanthan Gum, Citrus Aurantium Dulcis (Orange) Peel Extract, Salicylic Acid, Citrus Paradisi (Grapefruit) Extract, Benzyl Alcohol, Aniba Rosodora (Rosewood) Wood Extract, Citrus Aurantifolia (Lime) Peel Extract, Vanilla Planifolia Fruit Extract, Potassium Sorbate, Citrus Medica Limonum (Lemon) Peel Oil*, Alumina, Octyldodecanol, Cananga Odorata Flower Oil*, Trihydroxystearin, Stearic Acid, Sorbic Acid, Water (Aqua), Acmella Oleracea Extract, Fagus Sylvatica Bud Extract*, Tocopherol (Vitamin E), CI 77891, CI 77492, CI 77499, CI 77491.

*Certified organic .

Questions or Comments?

1-800-263-8888

Outside Canada or the United States dial 514-333-8282 or visit www.nellydevuyst.com